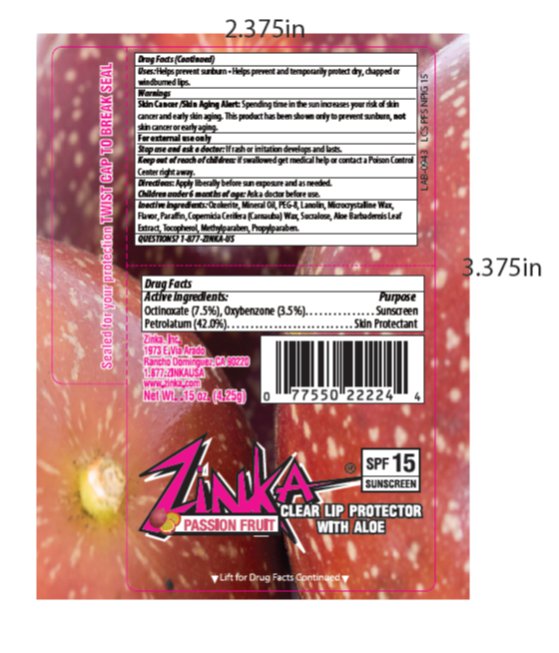 DRUG LABEL: Zinka Passion Fruit SPF 15 Lip Balm
NDC: 52993-111 | Form: STICK
Manufacturer: Zinka
Category: otc | Type: HUMAN OTC DRUG LABEL
Date: 20140509

ACTIVE INGREDIENTS: OCTINOXATE 7.5 mg/1 g; OXYBENZONE 3.5 mg/1 g; PETROLATUM 42 mg/1 g
INACTIVE INGREDIENTS: LIGHT MINERAL OIL 13.00 mg/1 g; MICROCRYSTALLINE WAX 3.00 mg/1 g; LANOLIN 3 mg/1 g; CERESIN 17 mg/1 g; PEG-8 STEARATE 5 mg/1 g

Drug Facts

Active ingredient

Octinoxate (7.5%), Oxybenzone (3.5%)

Petrolatum (42%)

Purpose

Sunscreen, Sunscreen, Skin Protectant

Keep Out of Reach of Children

If swallowed get medical help or contact a Poison Control Center right away.

Uses

Helps prevent sunburn. Helps prevent and temporarily protects dry, chapped or windburned lips.

Warnings

Skin Cancer/Skin Aging Alert: Spending time in the sun increases your risk of skin cancer and early skin aging. This product has been shown only to prevent sunburn, not skin cancer or early aging.

For external use only: Stop use and ask a doctor: if rash or irritation develops and lasts.

Directions

Apply liberally before sun exposure and as needed. Children under 6 months of age: Ask a doctor before use.

Inactive Ingredients

Ozokerite, Mineral Oil, PEG-8, Lanolin, Microcrystalline Wax, Flavor, Paraffin Wax, Copernicia Cerifera (Carnauba) Wax, Sucralose, Aloe Barbadenis Leaf Extract, Tocopherol, Methylparaben, Propylparaben.